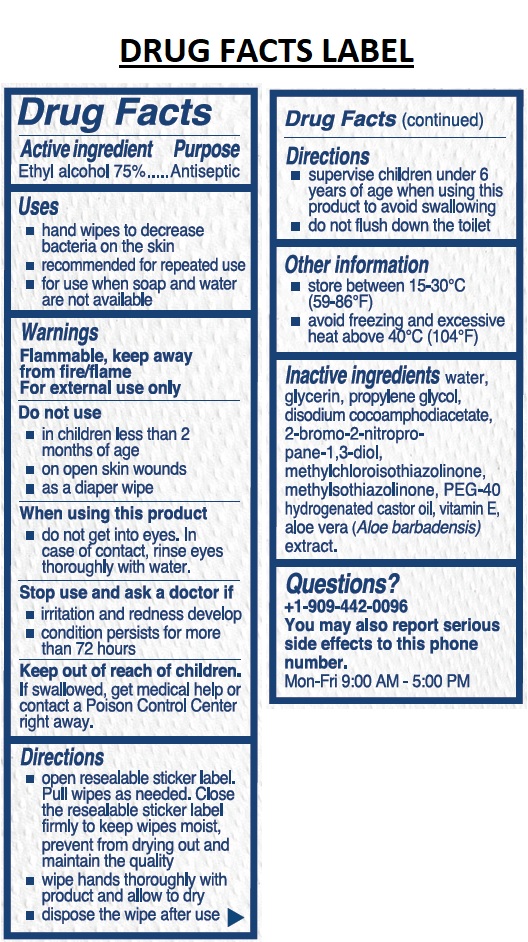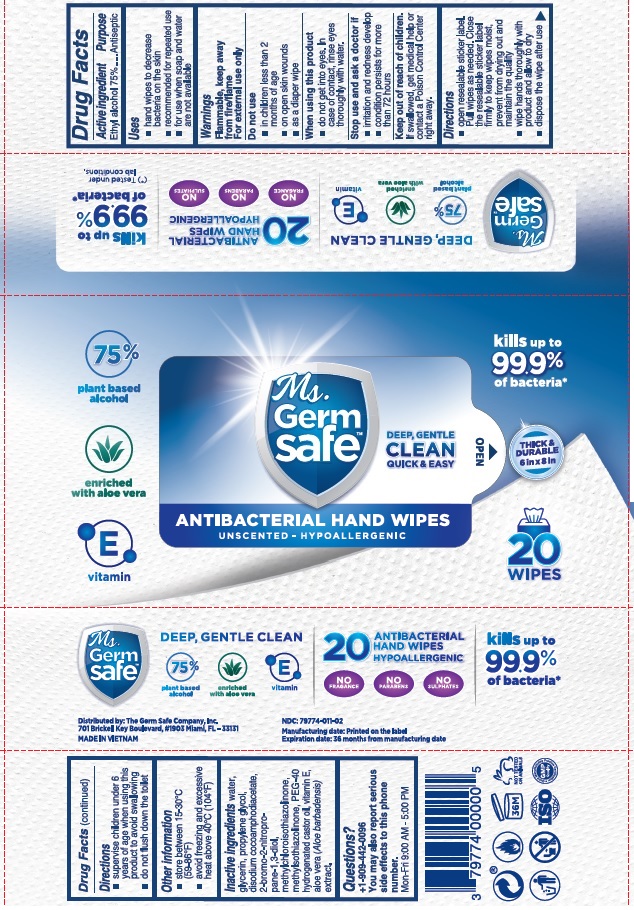 DRUG LABEL: Ms. Germsafe Antibacterial hand wipes
NDC: 79774-011 | Form: CLOTH
Manufacturer: Germ Safe Company, Inc., The
Category: otc | Type: HUMAN OTC DRUG LABEL
Date: 20220127

ACTIVE INGREDIENTS: ALCOHOL 75 mL/100 mL
INACTIVE INGREDIENTS: WATER; GLYCERIN; PROPYLENE GLYCOL; DISODIUM COCOAMPHODIACETATE; BRONOPOL; METHYLCHLOROISOTHIAZOLINONE; METHYLISOTHIAZOLINONE; POLYOXYL 40 HYDROGENATED CASTOR OIL; .ALPHA.-TOCOPHEROL; ALOE VERA LEAF

Ms.Germsafe™ ANTIBACTERIAL HAND WIPES

Active ingredient

Ethyl alcohol 75%

Purpose

Antiseptic

Uses

• hand wipes to decrease bacteria on the skin

• recommended for repeated use

• for use when soap and water are not available

Warnings

Flammable, keep away from fire/flame

For external use only

Do not use

• in children less than 2 months of age

• on open skin wounds

• as a diaper wipe

When using this product

• do not get into eyes. In case of contact, rinse eyes thoroughly with water.

Stop use and ask a doctor if

• irritation and redness develop

• condition persists for more than 72 hours

Keep out of reach of children.

If swallowed, get medical help or contact a Poison Control Center right away.

Directions

• open resealable sticker label. Pull wipes as needed. Close the resealable sticker label firmly to keep wipes moist, prevent from drying out and maintain the quality

• wipe hands thoroughly with product and allow to dry

• dispose the wipe after use

• supervise children under 6 years of age when using this product to avoid swallowing

• do not flush down the toilet

Other information

• store between 15-30˚C (59-86˚F)

• avoid freezing and excessive heat above 40˚C (104˚F)

INACTIVE INGREDIENT

Inactive ingredients water, glycerin, propylene glycol, disodium cocoamphodiacetate, 2-bromo-2-nitropropane-1,3-diol, methychloroisothiazolinone, methylisothiazolinone, PEG-40 hydrogenated castor oil, vitamin E, aloe vera (Aloe barbadensis) extract.

Questions?

+1-909-442-0096

You may also report serious side effects to this phone number.

Mon-Fri 9:00 AM - 5:00 PM

kills up to 99.9% of bacteria*

THICK & DURABLE

DEEP, GENTLE CLEAN QUICK & EASY

UNSCENTED - HYPOALLERGENIC

75% plant based alcohol

enriched with aloe vera

vitamin E

NO FRAGRANCE

NO PARABEN

NO SULPHATES

(*) Tested under lab conditions.

Distributed by: The Germ Safe Company, Inc.

701 Brickell Key Boulevard, #1903 Miami, FL -33131

MADE IN VIETNAM

Manufacturing date: Printed on the label

Expiration date: 36 months from manufacturing date

NOT TESTED ON ANIMALS

ISO

GMP